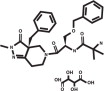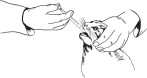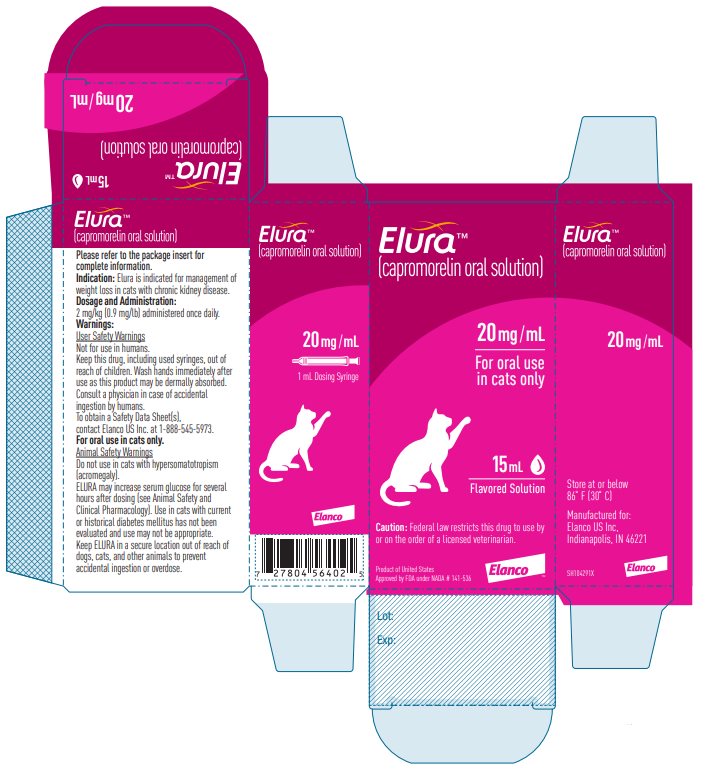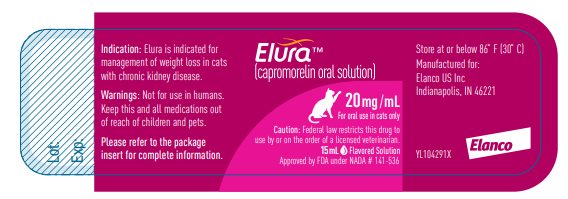 DRUG LABEL: Elura
NDC: 58198-5545 | Form: SOLUTION
Manufacturer: Elanco US Inc.
Category: animal | Type: PRESCRIPTION ANIMAL DRUG LABEL
Date: 20251111

ACTIVE INGREDIENTS: Capromorelin 20 mg/1 mL

Elura™

(capromorelin oral solution)

20 mg/mL

For oral use in cats only

CAUTION:

Federal law restricts this drug to use by or on the order of a licensed veterinarian.

DESCRIPTION:

ELURA (capromorelin oral solution) is a colorless to yellow or orange, clear liquid. Each milliliter of ELURA contains 20 mg of capromorelin tartrate. The empirical formula is C28H35N5O4·C4H6O6 and the molecular weight 655.70. The chemical name is 2-amino-N-[2-(3aR-benzyl-2-methyl-3-oxo-2,3,3a,4,6,7-hexahydro-pyrazolo[4,3-c]pyridine-5-yl)-1R-benzyloxymethyl-2-oxo-ethyl]-isobutyramide L-tartrate. The chemical structure of capromorelin tartrate is:

INDICATION:

For management of weight loss in cats with chronic kidney disease.

DOSAGE AND ADMINISTRATION:

Administer ELURA orally at a dose of 2 mg/kg (0.9 mg/lb) or 0.1 mL/kg (0.045 mL/lb) body weight once daily.

To administer ELURA:

- Remove the cap, insert the dosing syringe, invert the bottle, withdraw the appropriate amount of solution.
- Return the bottle to the upright position, remove syringe, replace the cap.
- Administer the solution into the cat's mouth.
- Rinse the syringe and plunger with water and leave apart to dry.

If the cat is routinely fed meals, offer food 30 minutes after administering the dose.

If the cat vomits within 15 minutes or only receives a partial dose, then the dose may be re-administered.

CONTRAINDICATIONS:

ELURA should not be used in cats that have a hypersensitivity to capromorelin.

WARNINGS:

User Safety Warnings

Not for use in humans. Keep this drug, including used syringes, out of reach of children.

Wash hands immediately after use as this product may be dermally absorbed.

Consult a physician in case of accidental ingestion by humans.

To obtain a Safety Data Sheet(s), contact Elanco US Inc. at 1-888-545-5973.

For oral use in cats only.

Animal Safety Warnings

Do not use in cats with hypersomatotropism (acromegaly).

ELURA may increase serum glucose for several hours after dosing (see Animal Safety and Clinical Pharmacology). Use in cats with current or historical diabetes mellitus has not been evaluated and use may not be appropriate.

Keep ELURA in a secure location out of reach of dogs, cats, and other animals to prevent accidental ingestion or overdose.

PRECAUTIONS:

Use with caution in cats that may have cardiac disease or severe dehydration. ELURA causes transient decreases in heart rate and blood pressure up to 4 hours following dose administration. Some cats may exhibit clinical signs of bradycardia or hypotension following administration of ELURA. (See Adverse Reactions and Animal Safety).

Use with caution in cats with hepatic dysfunction. Capromorelin is metabolized in the liver in humans and dogs and similar metabolism is expected in the cat.

The safe use of ELURA has not been evaluated in cats younger than 5 months old.

The safe use of ELURA has not been evaluated in cats that are pregnant, lactating, or intended for breeding.

ADVERSE REACTIONS:

Safety was evaluated in a 56-day field effectiveness study in 176 client-owned cats (118 administered ELURA, 58 administered vehicle control) that received at least one dose.

Cats enrolled had ≥5% unintended weight loss and a history of chronic kidney disease (CKD). Cats had a mean age of 15 years and at enrollment 11.4% of the cats were in Stage 1 CKD, 66.5% were in Stage 2, 21.0% were in Stage 3, and 1.1% were in Stage 4.

Cats enrolled in the study had a variety of comorbid conditions: dental disease (88.1%), moderate or severe muscle loss (43.2%), heart murmur (28.4%), history of vomiting or underlying gastrointestinal disease (28.4%), hyperthyroidism (13.6%) and hypertension (9.7%).

Table 1: Adverse Reactions in the Field Effectiveness Study
Adverse Reaction | ELURA (n=118) | Vehicle Control (n=58)
Vomiting | 35 (29.6%) | 13 (22.4%)
Hypersalivation | 25 (21.2%) | 0 (0.0%)
Inappetence | 22 (18.6%) | 7 (12.0%)
Behavior Change a | 17 (14.4%) | 3 (5.2%)
Lethargy | 16 (13.6%) | 6 (10.3%)
Anemia | 11 (9.3%) | 1 (1.7%)
Dehydration | 11 (9.3%) | 2 (3.4%)
Stage of CKD Increased b | 10 (8.5%) | 3 (5.2%)
Diarrhea | 9 (7.6%) | 2 (3.4%)
Urinary Tract Infection | 8 (6.8%) | 2 (3.4%)
Hyperglycemia | 8 (6.8%) | 2 (3.4%)
Upper Respiratory Infection | 7 (5.9%) | 1 (1.7%)
Hypercalcemia | 7 (5.9%) | 0 (0.0%)
Facial Skin Lesion | 6 (5.1%) | 3 (5.2%)
Hyperkalemia | 5 (4.2%) | 0 (0.0%)
Ataxia | 4 (3.4%) | 0 (0.0%)
Diabetes Mellitus | 1 (0.8%) | 0 (0.0%)
Congestive Heart Failure | 1 (0.8%) | 0 (0.0%)
Note: If an animal experienced the same event more than once, only the first occurrence was tabulated.
a Behavior change included hiding from the owner (8 ELURA, 1 vehicle control); owner reported difficulty administering medication (7 ELURA, 1 vehicle control); and redirected aggression to another household cat (2 ELURA, 1 vehicle control).
b Two ELURA and 1 vehicle control cat increased by two CKD stages; 8 ELURA and 2 vehicle control cats increased one CKD stage. It could not be determined if the progressive renal disease was the natural course of the pre-existing disease or treatment related.

Hypersalivation was generally associated with dosing and resolved within a few minutes.

Nine cats (8 ELURA and 1 vehicle control) either died or were euthanized during or shortly after the study. Six ELURA cats were euthanized or died from decompensated CKD. One ELURA cat was euthanized after study withdrawal on Day 33 for declining quality of life and recent identification of a new mass. One ELURA cat acutely declined and was euthanized for findings of nodules in both kidneys and diagnosis of sarcoma. The vehicle control cat was euthanized for acute onset of right hindlimb paresis and suspected embolic event. Two additional cats were diagnosed with neoplasia during the study (one ELURA cat with unspecified soft tissue sarcoma and one control cat with mammary adenocarcinoma) but completed the study.

Post-Approval Experience (2025)

The following adverse events are based on post-approval adverse drug experience reporting for ELURA. Not all adverse events are reported to FDA/CVM. It is not always possible to reliably estimate the adverse event frequency or establish a causal relationship to product exposure using these data.

The following adverse events in cats are categorized in order of decreasing reporting frequency by body system and in decreasing order of reporting frequency within each body system:
Gastrointestinal: hypersalivation, vomiting
General: lethargy, anorexia, recumbency, weakness
Behavioral: unusual behaviors, hiding, vocalization, hyperactivity
Cardiovascular: bradycardia, hypotension
Neurological: loss of consciousness, sedation
Respiratory: dyspnea

CONTACT INFORMATION:

To report suspected adverse drug experiences, contact Elanco US Inc. at 1-888-545-5973.

For additional information about reporting adverse drug experiences for animal drugs, contact FDA at 1-888-FDA-VETS or http://www.fda.gov/reportanimalae.

INFORMATION FOR CAT OWNERS:

Owners should be advised that ELURA mimics the action of a naturally-occurring hormone called ghrelin. Ghrelin influences many systems in the body. ELURA may also affect these systems.

Owners should monitor for changes in: thirst or water intake; lethargy or weakness; digestive issues (vomiting, diarrhea, drooling, decreased appetite); or behaviors.

CLINICAL PHARMACOLOGY:

Mechanism of Action

ELURA is a selective ghrelin receptor agonist. The ghrelin receptor is found in many tissues in various species and may have effects in the central nervous system, gastrointestinal tract, cardiovascular system and energy homeostasis. ELURA binds to receptors in the hypothalamus to stimulate appetite and in the pituitary to stimulate secretion of growth hormone (GH). Increased GH stimulates release of insulin like growth factor 1 (IGF-1) from the liver, which in turn can stimulate weight gain. IGF-1 remains elevated during administration of the drug.

In humans, IGF-1 elevation may act as a negative feedback regulator of GH, but this is unknown in cats. The clinical effects of ELURA in cats are thought to be due to a combination of increased food intake and metabolic changes resulting in weight gain.

Pharmacokinetics

The pharmacokinetic parameters of capromorelin were evaluated in a cross-over study in 4 male and 8 female laboratory cats receiving a single oral dose of ELURA at 2 mg/kg in the fed or fasted state. Following 8 hours of fasting, half the cats were fed a meal of canned food 30 minutes before dosing and the others continued to be fasted until 4 hours post ELURA administration. Blood samples were collected prior to dosing (pre-feeding) and at 0.25, 0.5, 1, 2, 4, 6, 8, 12, and 24 hours post-dosing for determination of serum capromorelin concentrations. Serum concentrations of capromorelin were measured using a liquid chromatography with mass spectrometry detection method. Blood samples were collected prior to dosing (pre-feeding) and at 8, 12, and 24 h post-dosing for determination of serum IGF-1.

Table 2. Mean (Standard Deviation) Pharmacokinetic Parameters for Serum Capromorelin
Parameter | Fasted | Fed
Tmaxa (hr) | 0.25 (0.25-1) (n=10) | 0.75 (0.5-4) (n=6)
Cmax (ng/mL) | 59 ± 42 (n=10) | 28 ± 20 (n=6)
AUClast (ng*hr/mL) | 83 ± 42 (n=10) | 51 ± 21 (n=6)
T½ (hr) | 1.12 ± 0.16 (n=8) | NAb
Data were analyzed for only 10 and 6 cats in the fasted and fed groups respectively, because there was an insufficient number of quantifiable serum concentrations for analysis.
aMedian and Range
bInsufficient data to calculate mean and standard deviation for T½
Tmax = time to maximum serum concentration
Cmax =maximum serum concentration
AUClast = area under the curve from the time of dosing to the last quantifiable serum concentration
T½= half-life
Capromorelin was rapidly absorbed following oral administration of ELURA to fasted cats. The Cmax and AUClast for capromorelin were 55% and 43% lower, respectively, in the fed state, as compared to the fasted state. Serum IGF-1 values did not appear to be affected by the feeding state.

EFFECTIVENESS:

Effectiveness was demonstrated in a multicenter, prospective, masked, randomized, vehicle-controlled field study. The study enrolled 176 client-owned cats with ≥5% unintended weight loss and a history of chronic kidney disease. The cats enrolled included 96 females and 80 males of various breeds, 4.4 - 22.1 years old with a mean age of 15 years and weighing 1.81 - 6.76 kg. CKD stage was determined based on creatinine at screening according to the International Renal Interest Society (IRIS) 2015 guidelines. All stages were enrolled. Cats were administered ELURA at 2 mg/kg or a matched volume of control once daily by mouth for 56 days. The control was the solution without capromorelin (vehicle control). The primary effectiveness variable was the percent change in body weight from Day 0 to Day 55. Effectiveness was evaluated in 112 cats: 71 cats administered ELURA and 41 cats administered vehicle control. There was a statistically significant difference between the percent change in weight for the ELURA group (+5.2%) compared to the vehicle control group (-1.6%) at Day 55 (p<0.0001). Secondary analysis for percent change in weight at Day 15 and Day 27 demonstrated cats in the ELURA group gained weight throughout the study.

Table 3. Least Squares Mean (Standard Error) Percent Change in Weight from Day 0
Study Day | ELURA | Vehicle Control | Difference (ELURA-Vehicle Control)
Day 15 | +3.3% (0.4) | 0.0% (0.5) | +3.3% (0.6)
Day 27 | +3.8% (0.6) | -0.9% (0.7) | +4.7% (0.8)
Day 55a | +5.2% (0.8) | -1.6% (1.0) | +6.8% (1.2)
a Primary endpoint

TARGET ANIMAL SAFETY:

Margin of Safety Laboratory Study

In a 6-month laboratory study, 32 healthy cats (4 cats/sex/group) approximately 11 months of age were dosed orally once daily in the fasted state with placebo control (0.5 mL/kg water) or ELURA at 2.1 mg/kg (1X), 6.3 mg/kg (3X) or 10.5 mg/kg (5X). Two cats died during the study. One male in the 10.5 mg/kg group died due to urethral obstruction on Day 23; this was unrelated to ELURA administration. One male in the 10.5 mg/kg group developed hyperglycemia and glucosuria on Day 30. This cat was euthanized for clinical decline associated with diabetic ketoacidosis on Day 50.

Administration of ELURA resulted in increased body weight (all groups) and increased food consumption (6.3 and 10.5 mg/kg groups). Salivation and intermittent vomiting were observed in placebo and all groups administered ELURA, more frequently in males, and increased in the groups administered ELURA in a dose-dependent manner. The following were observed more frequently in cats in the groups administered ELURA: increased mean corpuscular volume (MCV), increased triglycerides, and soft feces.

The following were observed only in cats in the groups administered ELURA: decreased lymphocyte count, decreased hematopoietic cellularity of the bone marrow, focal necrosis of the bone marrow, and mononuclear cell infiltration of the liver. The following changes were observed as trends in groups administered ELURA, although individual values remained within the reference intervals: decreased mean erythrocyte counts, mean hemoglobin concentrations, and mean hematocrits. There were no clinically relevant treatment-related effects on organ weights.

Laboratory Cardiovascular and Blood Glucose Safety Study

A 32-day laboratory study provided information on the cardiovascular and glycemic effects of ELURA in 8 healthy juvenile male cats. Cats had a telemetry device implant for continuous monitoring of cardiovascular variables and blood glucose. Cats were administered vehicle control once daily for 3 days (Days 1-3) followed by ELURA at 2 mg/kg once daily for 28 days (Days 4-31). ELURA administration resulted in transient decreases in heart rate which began after dosing, reached maximal suppression at approximately 1 hour post-dose (lowest individual value was 83 bpm) and returned to baseline within 4 hours. ELURA resulted in transient decreases in direct blood pressure (systolic, diastolic and mean arterial) which began after dosing, reached maximal suppression at approximately 1 hour post-dose (lowest individual value was 72 mmHg systolic) and returned to baseline within 4 hours. The effects on blood pressure were greatest following the first dose of ELURA and decreased in magnitude and frequency, returning to baseline after the ninth dose. The depressive effects of ELURA on heart rate and blood pressure were reversed when the cats were handled by study personnel. ELURA administration resulted in increased blood glucose in 4 cats, with individual variability in magnitude and duration. One cat had a maximum blood glucose of 296 mg/dL recorded 19 hours after the third dose, while values in all other cats remained <160 mg/dL at all times. The effects on glucose resolved after the eighth dose. ELURA administration resulted in increased serum IGF-1, with individual cat variability. Group mean serum IGF-1 was increased on Day 32 compared to the Day -3 baseline. On Day 27, group mean serum IGF-1 was increased 8 hours post-dosing compared to pre-dosing on the same day.

STORAGE CONDITIONS:

Store at or below 86˚F (30˚C)

HOW SUPPLIED:

20 mg/mL flavored oral solution in a 15 mL bottle with an oral dosing syringe.

Approved by FDA under NADA # 141-536.

Manufactured for: Elanco US Inc, Indianapolis, IN 46221 USA

REV. DATE-08/2025

ELURA, Elanco and the diagonal bar logo are trademarks of Elanco or its affiliates.

© 2025 Elanco or its affiliates

ElancoTM

PA104291X

Principal Display Panel - 15 mL Carton Label

Elura™

(capromorelin oral solution)

20 mg/mL

For oral use
in cats only

15 mL

Flavored Solution

Caution: Federal law restricts this drug to use by
or on the order of a licensed veterinarian.

Product of United States

Approved by FDA under NADA # 141-536

Elanco™

Principal Display Panel - 15 mL Bottle Label

Elura™

(capromorelin oral solution)

20 mg/mL

For oral use in cats only

Caution: Federal law restricts this drug to
use by or on the order of a licensed veterinarian.

15 mL Flavored Solution

Approved by FDA under NADA # 141-536